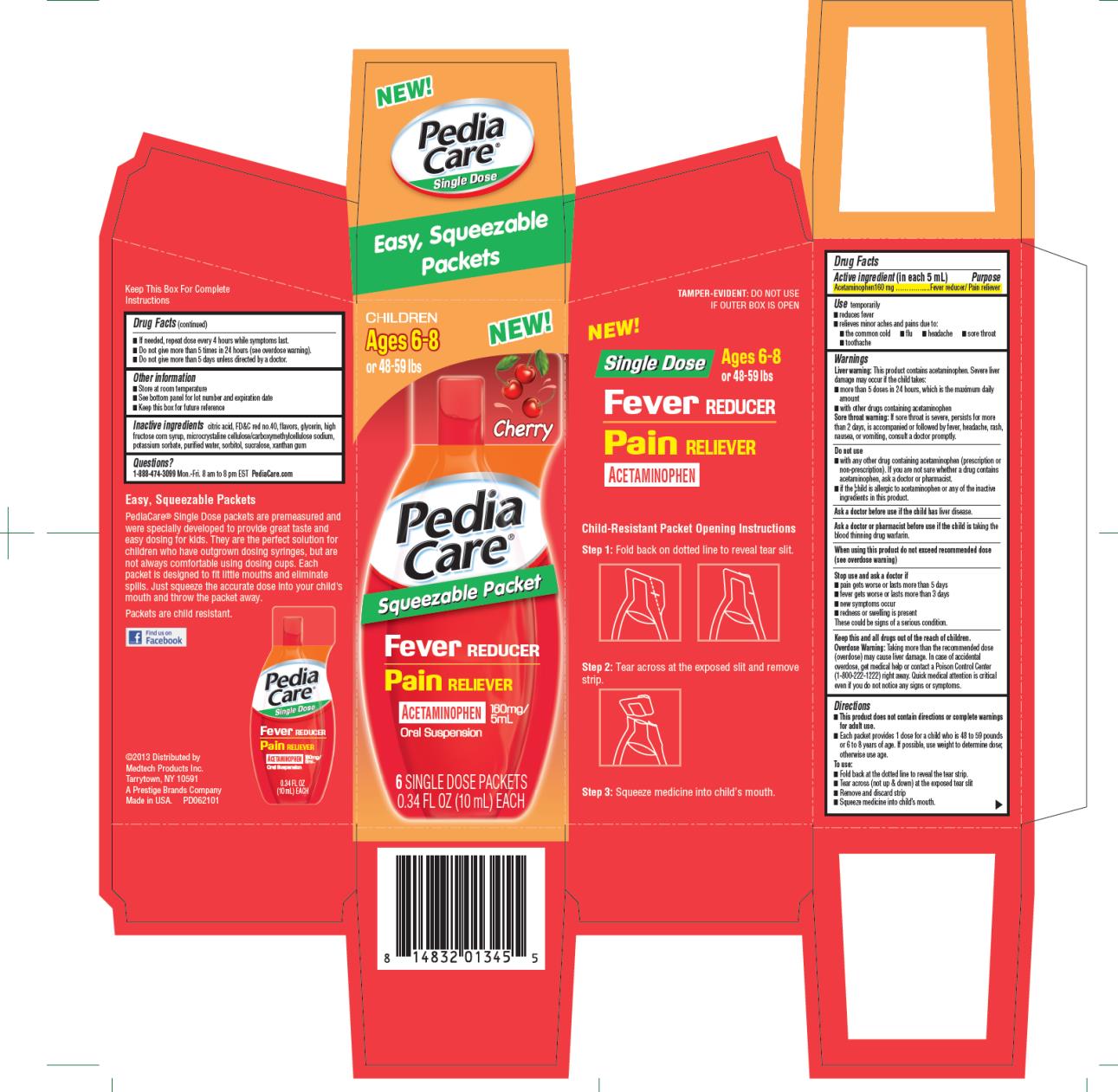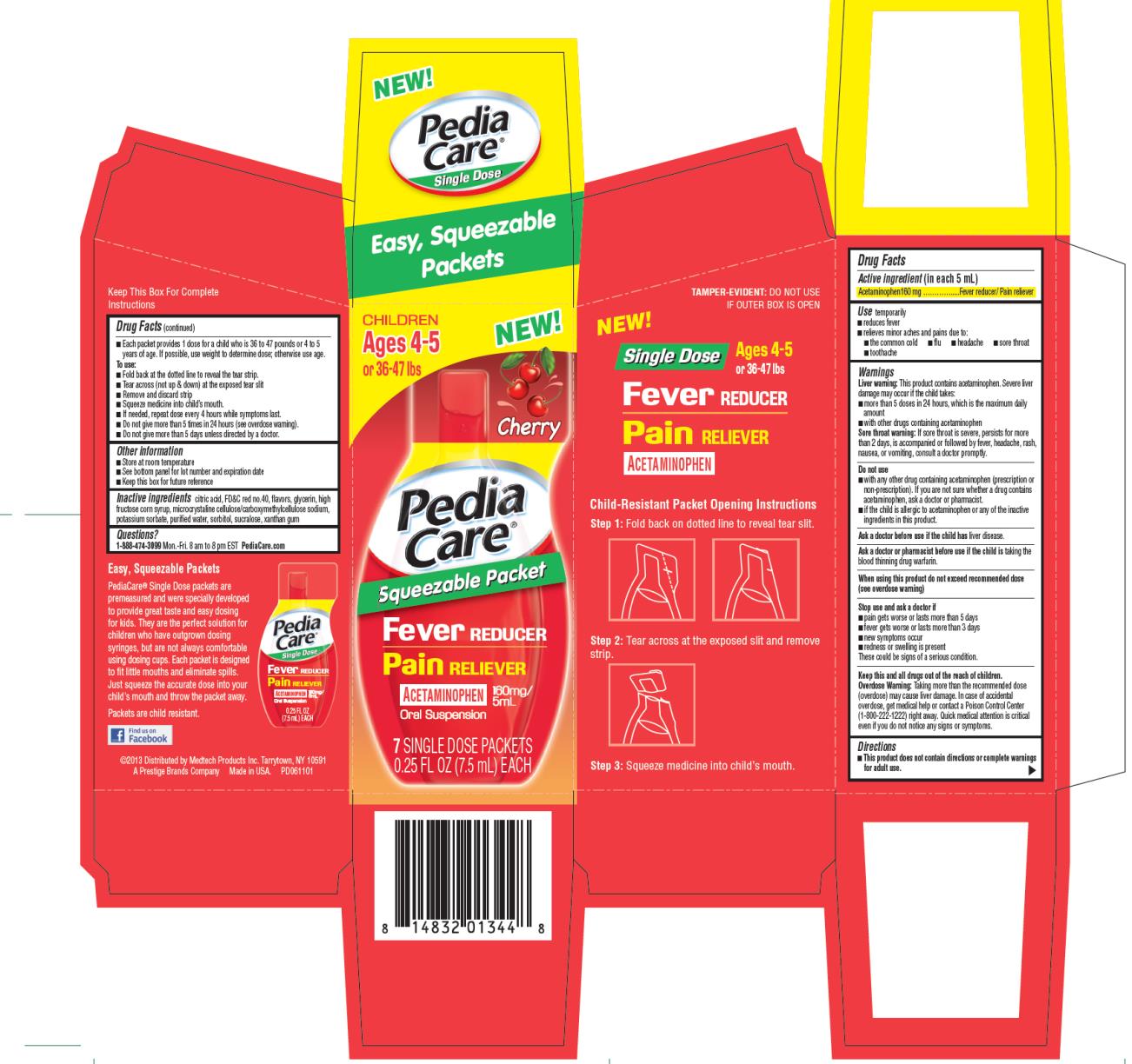 DRUG LABEL: PediaCare Single Dose Fever Reducer
NDC: 63029-075 | Form: LIQUID
Manufacturer: Medtech Products Inc.
Category: otc | Type: HUMAN OTC DRUG LABEL
Date: 20130715

ACTIVE INGREDIENTS: ACETAMINOPHEN 160 mg/5 mL
INACTIVE INGREDIENTS: CITRIC ACID MONOHYDRATE; FD&C RED NO. 40; GLYCERIN; HIGH FRUCTOSE CORN SYRUP; CELLULOSE, MICROCRYSTALLINE; POTASSIUM SORBATE; WATER; SORBITOL; XANTHAN GUM; SUCRALOSE

PediaCare Single Dose Fever Reducer

CHILDREN
Ages 6-8 NEW!
or 48-59 lbs

Drug Facts

Active ingredient

(in each 5 mL)

Acetaminophen 160 mg

Purpose

Fever reducer/pain reliever

Uses:

temporarily

- reduces fever
- relieves minor aches and pains due to:
  ○ the common cold
  ○ flu
  ○ headache
  ○ sore throat
  ○ toothache

Warnings

Liver warning: This product contains acetaminophen. Severe liver damage may occur if your child takes

- more than 5 doses in 24 hours, which is the maximum daily amount
- with other drugs containing acetaminophen

Sore throat warning: If sore throat is severe, persists for more than 2 days, is accompanied or followed by fever, headache, rash, nausea, or vomiting, consult a doctor promptly.

Do not use

- with any other drug containing acetaminophen (prescription or non-prescription). If you are not sure whether a drug contains acetaminophen, ask a doctor or pharmacist.
- if your child is allergic to acetaminophen or any of the inactive ingredients in this product.

Ask a doctor before use if your child has

liver disease.

Ask a doctor or pharmacist before use if your child is

taking the blood thinning drug warfarin.

When using this product

do not exceed recommended dosage (see overdose warning)

Stop use and ask a doctor if:

- pain gets worse or lasts for more than 5 days.
- fever gets worse or lasts for more than 3 days.
- new symptoms occur.
- redness or swelling is present.

These could be signs of a serious condition.

Keep out of reach of children.

Overdose warning. Taking more than the recommended dose (overdose) may cause liver damage. In case of accidental overdose, get medical help or contact a Poison Control Center (1-800-222-1222) right away. Quick medical attention is critical even if you do not notice any signs or symptoms.

Directions

• This product does not contain directions or complete warnings for adult use.

• Each packet provides 1 dose for a child who is 48 to 59 pounds or 6 to 8 years of age. If possible, use weight to determine dose; otherwise use age.

To use:

• Fold back at the dotted line to reveal the tear strip.

• Tear across (not up & down) at the exposed tear slit

• Remove and discard strip

• Squeeze medicine into child’s mouth.

• If needed, repeat dose every 4 hours while symptoms last.

• Do not give more than 5 times in 24 hours (see overdose warning).

• Do not give more than 5 days unless directed by a doctor.

Other information

• Store at room temperature

• See bottom panel for lot number and expiration date

• Keep this box for future reference

Inactive ingredients

citric acid, FD&C red no.40, flavors, glycerin, high fructose corn syrup, microcrystalline cellulose/carboxymethylcellulose sodium, potassium sorbate, purified water, sorbitol, sucralose, xanthan gum

Questions or comments?

1-888-474-3099 Mon.-Fri. 8 am to 8 pm EST PediaCare.com

PRINCIPAL DISPLAY PANEL

Children Ages 6-8
or 48-59 lbs
PediaCare Squeezable Packet
Fever Reducer
Pain Reliever
Acetaminophen
160mg/5mL
Oral Suspension
6 Single Dose Packets
0.34 FL OZ (10 mL) EACH

CHILDREN
Ages 4-5 NEW!
or 36-47 lbs

Drug Facts

Active ingredient

(in each 5 mL)

Acetaminophen 160 mg

Purpose

Fever reducer/pain reliever

Uses:

temporarily

- reduces fever
- relieves minor aches and pains due to:
  ○ the common cold
  ○ flu
  ○ headache
  ○ sore throat
  ○ toothache

Warnings

Liver warning: This product contains acetaminophen. Severe liver damage may occur if your child takes

- more than 5 doses in 24 hours, which is the maximum daily amount
- with other drugs containing acetaminophen

Sore throat warning: If sore throat is severe, persists for more than 2 days, is accompanied or followed by fever, headache, rash, nausea, or vomiting, consult a doctor promptly.

Do not use

- with any other drug containing acetaminophen (prescription or non-prescription). If you are not sure whether a drug contains acetaminophen, ask a doctor or pharmacist.
- if your child is allergic to acetaminophen or any of the inactive ingredients in this product.

Ask a doctor before use if your child has

liver disease.

Ask a doctor or pharmacist before use if your child is

taking the blood thinning drug warfarin.

When using this product

do not exceed recommended dosage (see overdose warning)

Stop use and ask a doctor if:

- pain gets worse or lasts for more than 5 days.
- fever gets worse or lasts for more than 3 days.
- new symptoms occur.
- redness or swelling is present.

These could be signs of a serious condition.

Keep out of reach of children.

Overdose warning. Taking more than the recommended dose (overdose) may cause liver damage. In case of accidental overdose, get medical help or contact a Poison Control Center (1-800-222-1222) right away. Quick medical attention is critical even if you do not notice any signs or symptoms.

Directions

• This product does not contain directions or complete warnings for adult use.

• Each packet provides 1 dose for a child who is 36 to 47 pounds or 4 to 5 years of age. If possible, use weight to determine dose; otherwise use age.

To use:

• Fold back at the dotted line to reveal the tear strip.

• Tear across (not up & down) at the exposed tear slit

• Remove and discard strip

• Squeeze medicine into child’s mouth.

• If needed, repeat dose every 4 hours while symptoms last.

• Do not give more than 5 times in 24 hours (see overdose warning).

• Do not give more than 5 days unless directed by a doctor.

Other information

• Store at room temperature

• See bottom panel for lot number and expiration date

• Keep this box for future reference

Inactive ingredients

citric acid, FD&C red no.40, flavors, glycerin, high fructose corn syrup, microcrystalline cellulose/carboxymethylcellulose sodium, potassium sorbate, purified water, sorbitol, sucralose, xanthan gum

Questions or comments?

1-888-474-3099 Mon.-Fri. 8 am to 8 pm EST PediaCare.com

PRINCIPAL DISPLAY PANEL

Children Ages 4-5
or 36-47 lbs
PediaCare Squeezable Packet
Fever Reducer
Pain Reliever
Acetaminophen
160mg/5mL
Oral Suspension
7 Single Dose Packets
0.25 FL OZ (7.5 mL) EACH